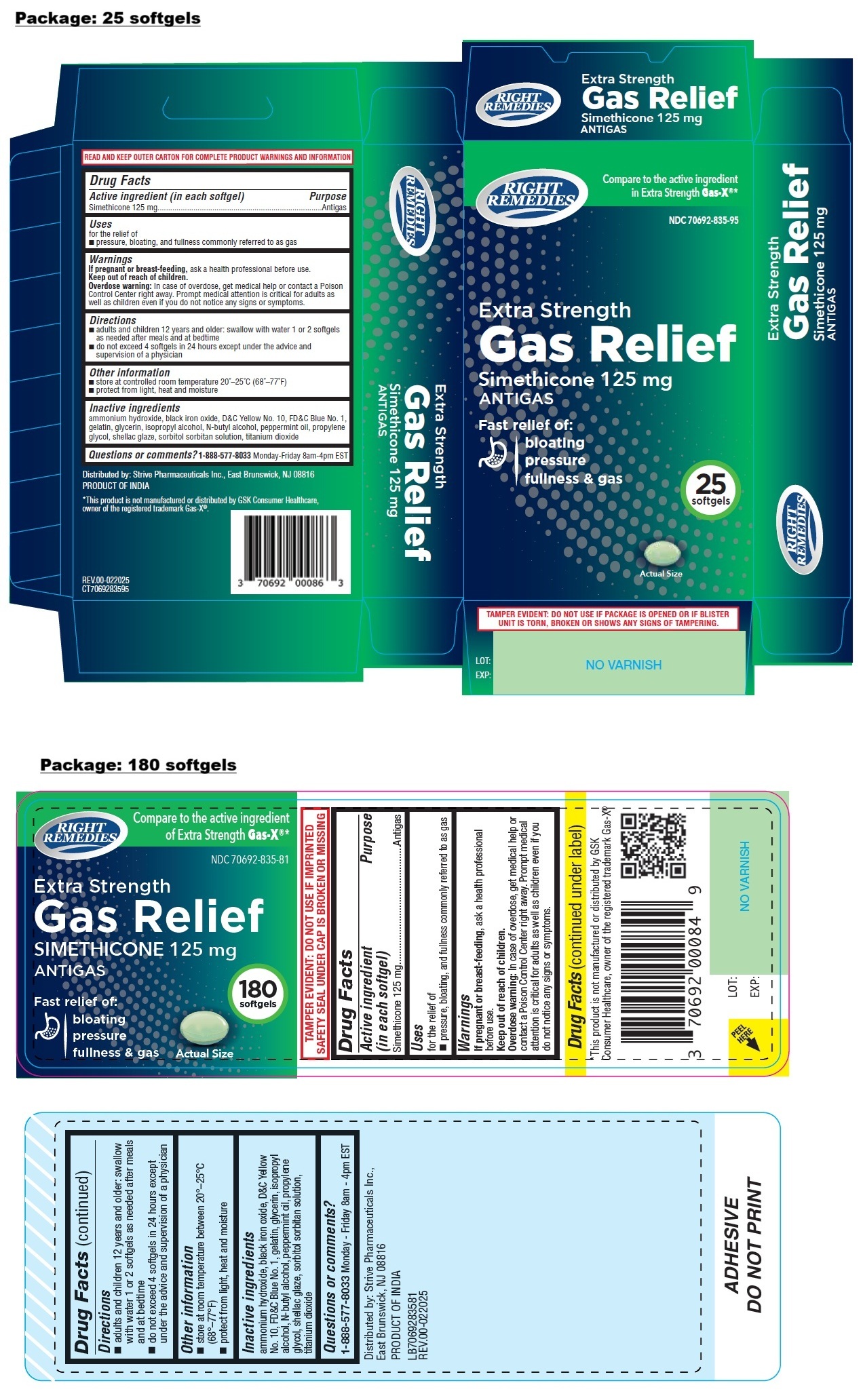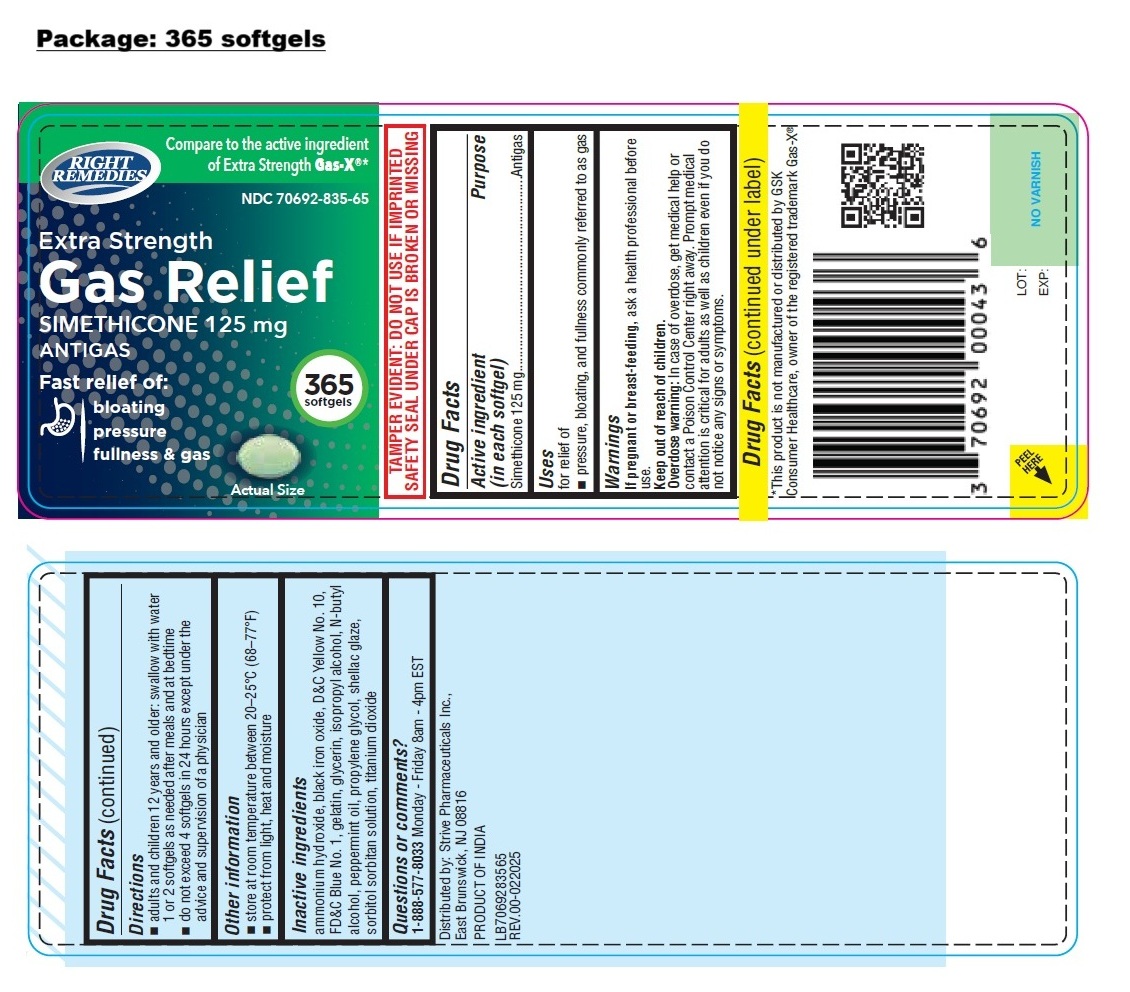 DRUG LABEL: RIGHT REMEDIES Extra Strength Gas Relief
NDC: 70692-835 | Form: CAPSULE, LIQUID FILLED
Manufacturer: Strive Pharmaceuticals Inc.
Category: otc | Type: HUMAN OTC DRUG LABEL
Date: 20250508

ACTIVE INGREDIENTS: DIMETHICONE, UNSPECIFIED 125 mg/1 1
INACTIVE INGREDIENTS: AMMONIA; FERROSOFERRIC OXIDE; D&C YELLOW NO. 10; FD&C BLUE NO. 1; GELATIN, UNSPECIFIED; GLYCERIN; ISOPROPYL ALCOHOL; BUTYL ALCOHOL; PEPPERMINT OIL; PROPYLENE GLYCOL; SHELLAC; SORBITOL; SORBITAN; TITANIUM DIOXIDE

RIGHT REMEDIES Extra Strength Gas Relief softgel

Active ingredient (in each softgel)

Simethicone 125 mg

Purpose

Antigas

Uses

for relief of
• pressure, bloating, and fullness commonly referred to as gas

Warnings

If pregnant or breast-feeding, ask a health professional before use.

Keep out of reach of children.
Overdose warning: In case of overdose, get medical help or contact a Poison Control Center right away. Prompt medical attention is critical for adults as well as children even if you do not notice any signs or symptoms.

Directions

• adults and children 12 years and older: swallow with water 1 or 2 softgels as needed after meals and at bedtime
• do not exceed 4 softgels in 24 hours except under the advice and supervision of a physician

Other information

• store at room temperature between 20–25°C (68–77°F)
• protect from light, heat and moisture

Inactive ingredients

ammonium hydroxide, black iron oxide, D&C Yellow No. 10, FD&C Blue No. 1, gelatin, glycerin, isopropyl alcohol, N-butyl alcohol, peppermint oil, propylene glycol, shellac glaze, sorbitol sorbitan solution, titanium dioxide

Questions or comments?

1-888-577-8033 Monday - Friday 8am - 4pm EST

Compare to the active ingredient of Extra Strength Gas-X®*

Fast relief of:
bloating
pressure
fullness & gas

TAMPER EVIDENT: DO NOT USE IF IMPRINTED SAFETY SEAL UNDER CAP IS BROKEN OR MISSING

*This product is not manufactured or distributed by GSK Consumer Healthcare, owner of the registered trademark Gas-X®

Distributed by: Strive Pharmaceuticals Inc.,
East Brunswick, NJ 08816

PRODUCT OF INDIA